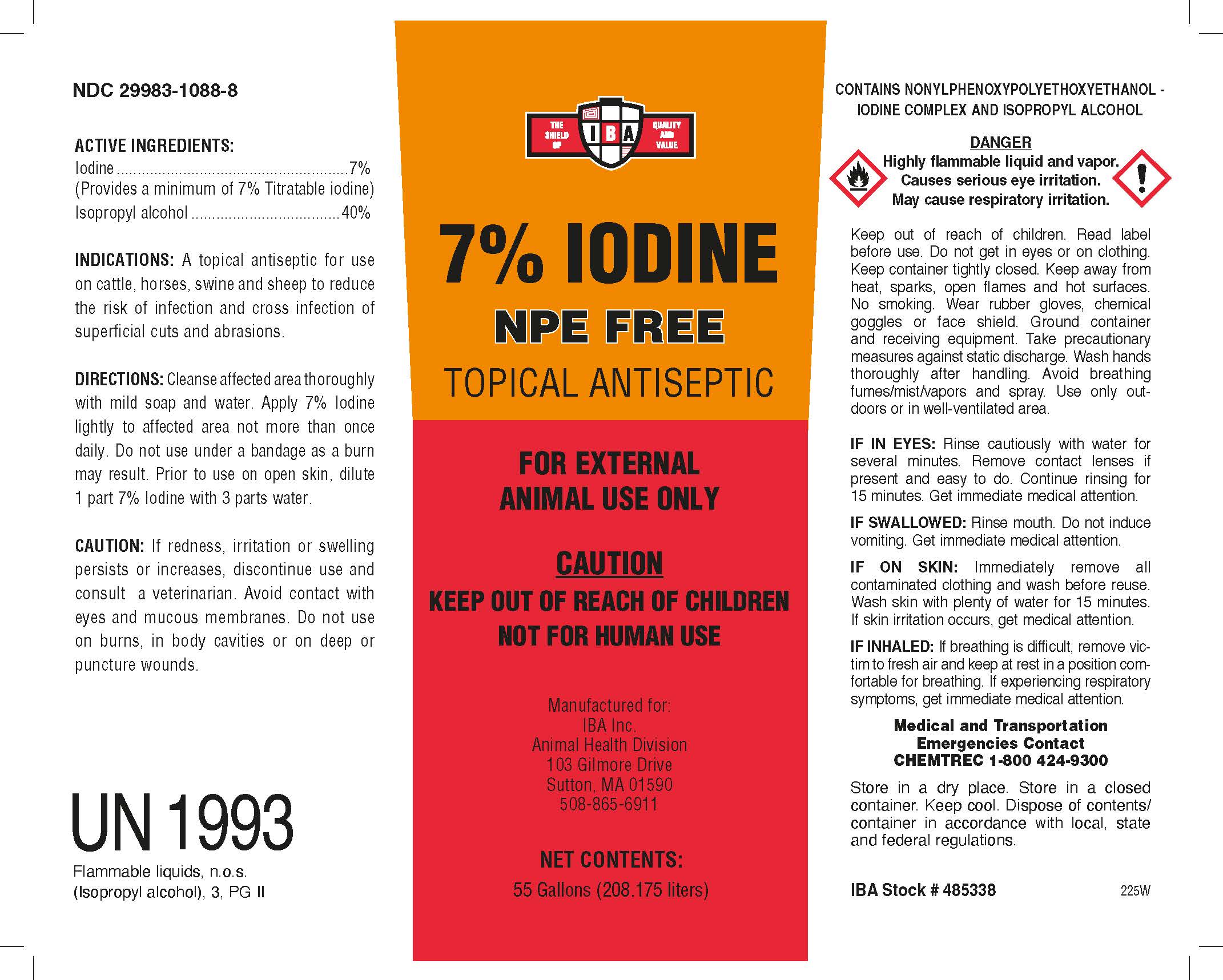 DRUG LABEL: 7% Iodine NPE Free Topical Antiseptic
NDC: 29983-1088 | Form: LIQUID
Manufacturer: IBA
Category: animal | Type: OTC ANIMAL DRUG LABEL
Date: 20251126

ACTIVE INGREDIENTS: IODINE 7.0 kg/100 kg; ISOPROPYL ALCOHOL 40.0 kg/100 kg

7% Iodine NPE Free Topical Antiseptic

ACTIVE INGREDIENT

Iodine Complex 36%

Isopropyl Alcohol 40%

Indications and Directions

Usage:

A topical antiseptic for use on catlle, horses, swine and sheep to reduce the risk of infectionand cross infection of superficial cuts and abrations.

Directions:

Cleanse affected area thoroughly with mild soap and water. Apply 7% Iodine lightly to affected area not more than once daily. Do not use under a bandage as a burn may result. Prior to use on open skin, dilute 1 part 7% iodine with 3 parts water.

Caution

If redness, irritation or swelling persists or increasis, discontinue use and consult a veterinarian. Avoid contact with eyes and mucous membranes. Do not use on burns, in body cavities or on deep pr punctured wounds.

Danger

Keep out of reach of children. Read label before use. Do not get in eyes or on clothing. Keep container tightly closed. Keep away from heat, sparks, open flames and hot surfaces. No smoking. Wear rubber gloves, chemical googles or face shield. Ground container and receiving equipment. Take precautionary measures against static discharge. Wash hands thoroughly after handling. Avoid breathing fumes/mist/vapors and spray. Use only outdoors or in well-ventilated area.

If in Eyes: Rinse cautionsly with water for several minutes.

Revome contact lenses if present and easy to do. Continue rinsing for 15 minutes. Get immediate medical attention.

If Swallowed: Rinse mouth. Do not induce vomiting. Get immediate medical attention.

If On Skin: Immediately remove all contaminated clothing and wash before reuse. Wash skin with plenty of water for 15minutes.

If skin irritation occurs, get medical attention.

If Inhaled: If breathing is difficult, remove victim to fresh air and keep at rest in a position comfortable for breathing. If experiencing respiratory symptoms, get immediete medical attention.